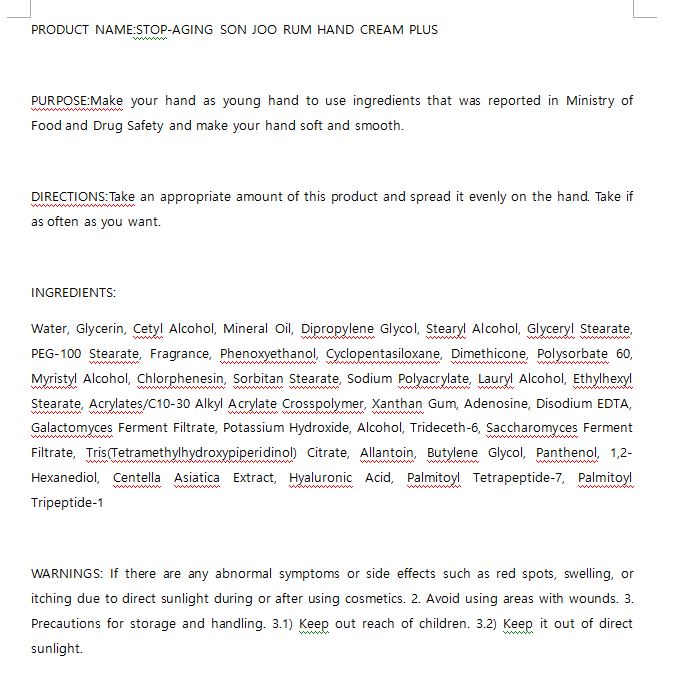 DRUG LABEL: W.SKIN STOP-AGING SON JOO RUM HANDCREAM PLUS
NDC: 74997-0013 | Form: CREAM
Manufacturer: J&J COMPANY
Category: otc | Type: HUMAN OTC DRUG LABEL
Date: 20210507

ACTIVE INGREDIENTS: CENTELLA ASIATICA 0.001 g/100 g
INACTIVE INGREDIENTS: GLYCERIN; WATER

J&J COMPANY - STOP-AGING PEPTIDE TONER

ACTIVE INGREDIENT

Centella Asiatica Extract

INACTIVE INGREDIENT

Water, Glycerin, Cetyl Alcohol, Mineral Oil, Dipropylene Glycol, Stearyl Alcohol, Glyceryl Stearate, PEG-100 Stearate, Fragrance, Phenoxyethanol, Cyclopentasiloxane, Dimethicone, Polysorbate 60, Myristyl Alcohol, Chlorphenesin, Sorbitan Stearate, Sodium Polyacrylate, Lauryl Alcohol, Ethylhexyl Stearate, Acrylates/C10-30 Alkyl Acrylate Crosspolymer, Xanthan Gum, Adenosine, Disodium EDTA, Galactomyces Ferment Filtrate, Potassium Hydroxide, Alcohol, Trideceth-6, Saccharomyces Ferment Filtrate, Tris(Tetramethylhydroxypiperidinol) Citrate, Allantoin, Butylene Glycol, Panthenol, 1,2-Hexanediol, Centella Asiatica Extract, Hyaluronic Acid, Palmitoyl Tetrapeptide-7, Palmitoyl Tripeptide-1

PURPOSE

Make your hand as young hand to use ingredients that was reported in Ministry of Food and Drug Safety and make your hand soft and smooth

keep out of reach of the children

INDICATIONS AND USAGE

Take an appropriate amount of this product and spread it evenly on the hand. Take if as often as you want.

WARNINGS

If there are any abnormal symptoms or side effects such as red spots, swelling, or itching due to direct sunlight during or after using cosmetics. 2. Avoid using areas with wounds. 3. Precautions for storage and handling. 3.1) Keep out reach of children. 3.2) Keep it out of direct sunlight. 4. Avoid spreading out around eyes.

DOSAGE AND ADMINISTRATION

for external use only